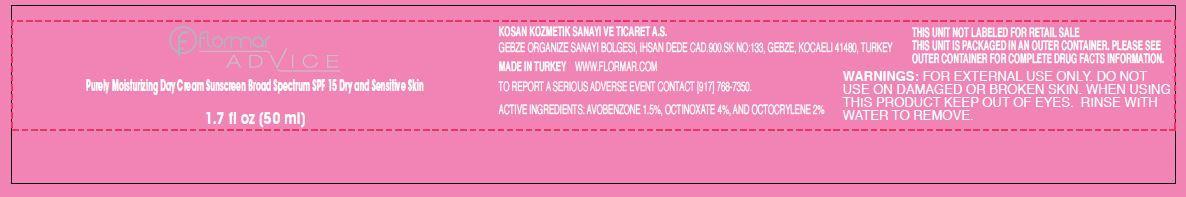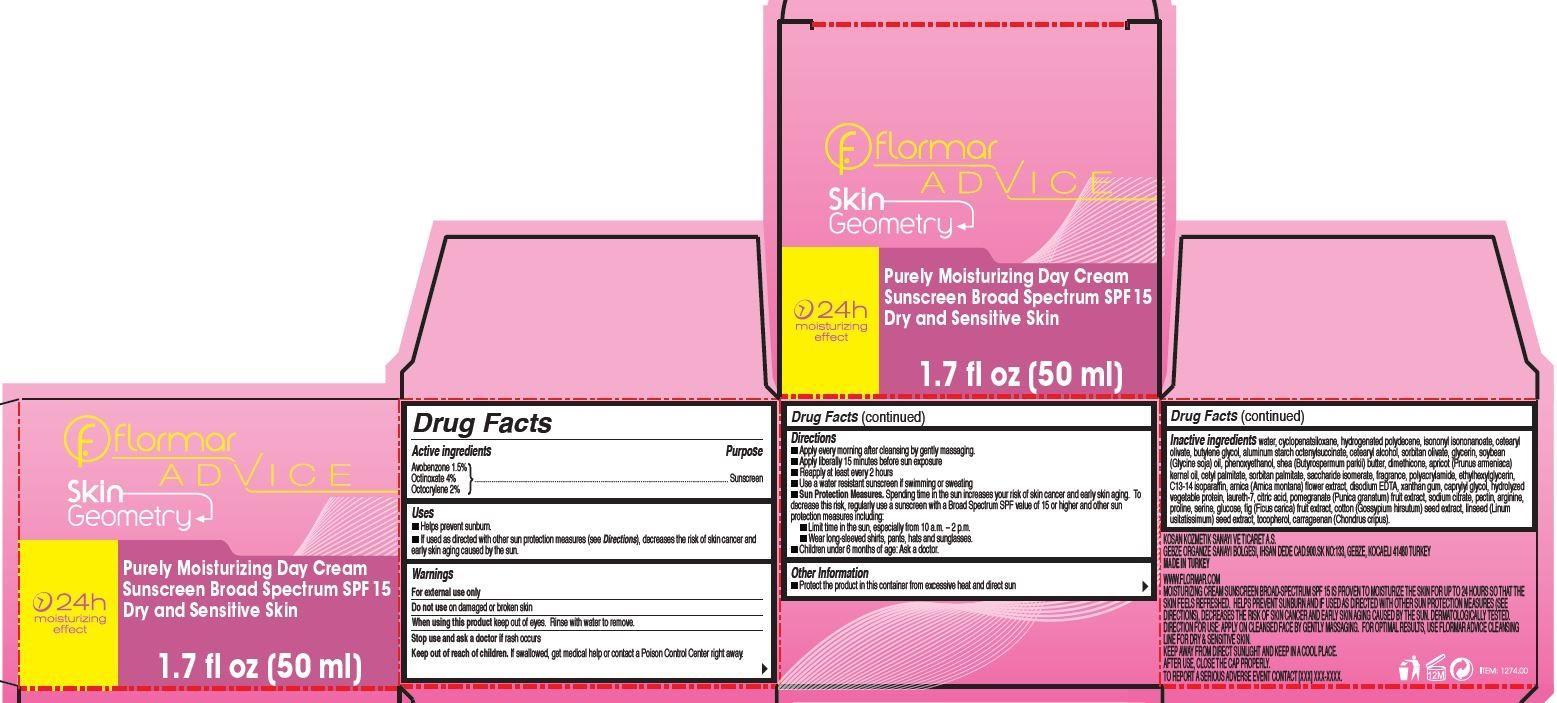 DRUG LABEL: flormar ADVICE Skin Geometry Purely Moisturizing Day Sunscreen Broad Spectrum SPF 15 Dry and Sensitive Skin
NDC: 61722-021 | Form: CREAM
Manufacturer: Kosan Kozmetik Sanayi ve Ticaret A.S.
Category: otc | Type: HUMAN OTC DRUG LABEL
Date: 20191018

ACTIVE INGREDIENTS: AVOBENZONE 15 mg/1 mL; OCTINOXATE 40 mg/1 mL; OCTOCRYLENE 20 mg/1 mL
INACTIVE INGREDIENTS: WATER; CYCLOMETHICONE 5; ISONONYL ISONONANOATE; CETEARYL OLIVATE; BUTYLENE GLYCOL; ALUMINUM STARCH OCTENYLSUCCINATE; CETOSTEARYL ALCOHOL; SORBITAN OLIVATE; GLYCERIN; SOYBEAN OIL; PHENOXYETHANOL; SHEA BUTTER; DIMETHICONE; APRICOT KERNEL OIL; CETYL PALMITATE; SORBITAN MONOPALMITATE; SACCHARIDE ISOMERATE; ETHYLHEXYLGLYCERIN; C13-14 ISOPARAFFIN; ARNICA MONTANA FLOWER; EDETATE DISODIUM; XANTHAN GUM; CAPRYLYL GLYCOL; LAURETH-7; CITRIC ACID MONOHYDRATE; POMEGRANATE; SODIUM CITRATE; PECTIN; ARGININE; PROLINE; SERINE; DEXTROSE; FIG; COTTON SEED; FLAX SEED; TOCOPHEROL; CARRAGEENAN; CHONDRUS CRISPUS

flormar ADVICE Skin Geometry Purely Moisturizing Day Cream Sunscreen Broad Spectrum SPF 15 Dry and Sensitive Skin

Active ingredients

Avobenzone 1.5%
Octinoxate 4%
Octocrylene 2%

Purpose

Sunscreen

Uses

- Helps prevent sunburn.
- If used as directed with other sun protection measures (see Directions), decreases the risk of skin cancer and early skin aging caused by the sun.

Warnings

For external use only

Do not use

on damaged or broken skin

When using this product

keep out of eyes. Rinse with water to remove.

Stop use and ask a doctor if

rash occurs

Keep out of reach of children.

If swallowed, get medical help or contact a Poison Control Center right away.

Directions

- Apply on cleansed face, neck and neckline by gently massaging every morning.
- Apply liberally 15 minutes before sun exposure
- Reapply at least every 2 hours
- Use a water resistant sunscreen if swimming or sweating
- Sun Protection Measures. Spending time in the sun increases your risk of skin cancer and early skin aging. To decrease this risk, regularly use a sunscreen with a Broad Spectrum SPF value of 15 or higher and other sun protection measures including:
- Limit time in the sun, especially from 10 a.m. – 2 p.m.
- Wear long-sleeved shirts, pants, hats and sunglasses.
- Children under 6 months of age: Ask a doctor.

Other Information

- Protect the product in this container from excessive heat and direct sun

Inactive ingredients

water, cyclopenatsiloxane, hydrogenated polydecene, isononyl isononanoate, cetearyl olivate, butylene glycol, aluminum starch octenylsuccinate, cetearyl alcohol, sorbitan olivate, glycerin, soybean (Glycine soja) oil, phenoxyethanol, shea (Butyrospermum parkii) butter, dimethicone, apricot (Prunus armeniaca) kernel oil, cetyl palmitate, sorbitan palmitate, saccharide isomerate, fragrance, polyacrylamide, ethylhexylglycerin, C13-14 isoparaffin, arnica (Arnica montana) flower extract, disodium EDTA, xanthan gum, caprylyl glycol, hydrolyzed vegetable protein, laureth-7, citric acid, pomegranate (Punica granatum) fruit extract, sodium citrate, pectin, arginine, proline, serine, glucose, fig (Ficus carica) fruit extract, cotton (Gossypium hirsutum) seed extract, linseed (Linum usitatissimum) seed extract, tocopherol, carrageenan (Chondrus cripus).